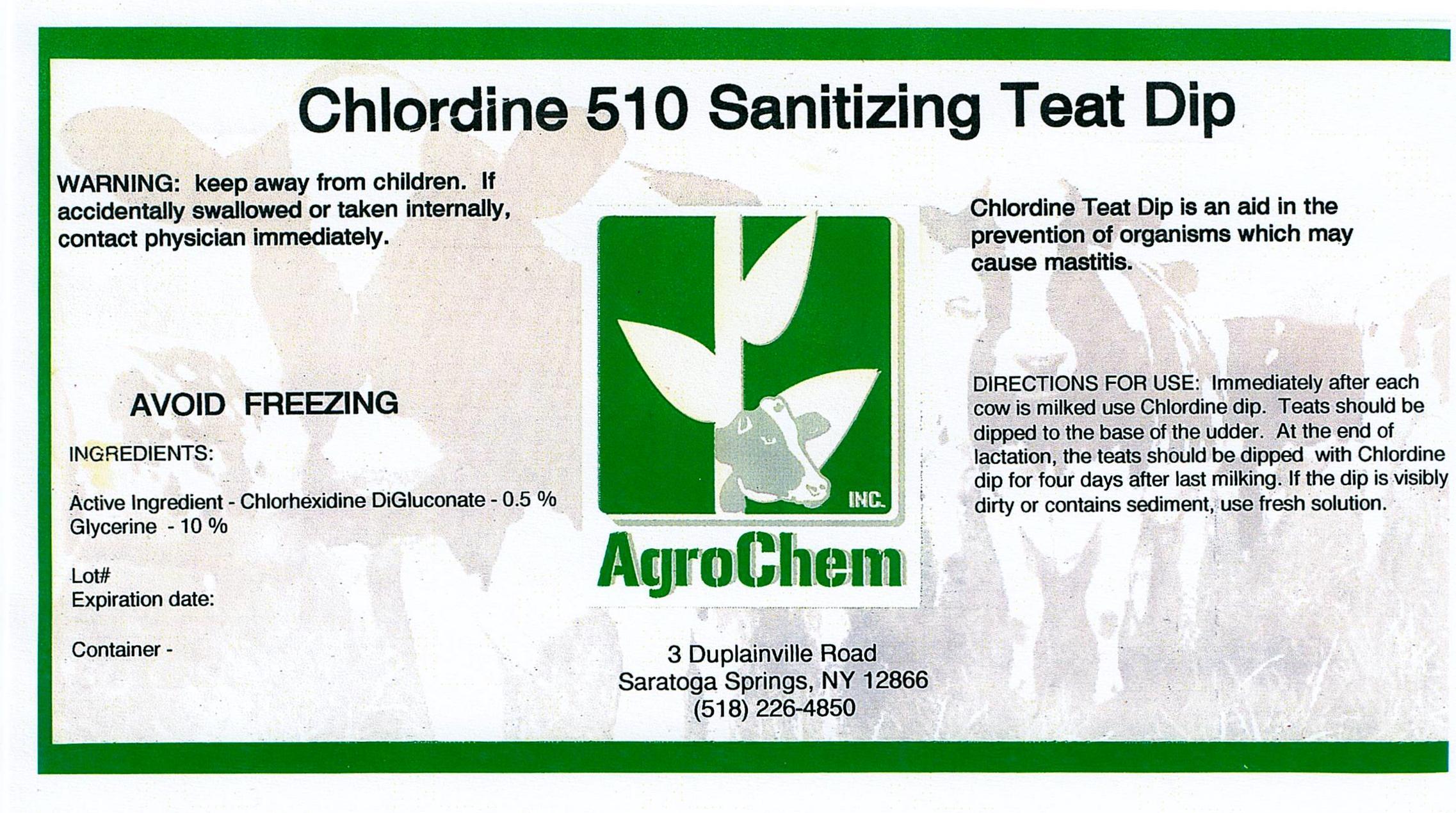 DRUG LABEL: Chlordine 510 Teat Dip
NDC: 17307-3323 | Form: SOLUTION
Manufacturer: AgroChem Inc
Category: animal | Type: OTC ANIMAL DRUG LABEL
Date: 20131029

ACTIVE INGREDIENTS: CHLORHEXIDINE GLUCONATE 0.005 kg/1 kg
INACTIVE INGREDIENTS: NONOXYNOL-12 0.01 kg/1 kg; GLYCERIN 0.10 kg/1 kg; HYDROXYETHYL CELLULOSE (4000 CPS AT 1%) 0.005 kg/1 kg

Chlordine 510 Teat Dip

WARNINGS

WARNING: keep away from children. If

accidentally swallowed or taken

internally, contact physician

immediately.

AVOID FREEZING

Active Ingredient - Chlorhexidine DiGluconate - 0.5%

Glycerine - 10%

DESCRIPTION

Chlordine Teat Dip is an aid in the

prevention of organisms which may

cause mastitis.

DIRECTIONS FOR USE: Immediately after each cow

is milked use Chlordine dip. Teats should be dipped

to the base of the udder. At the end of lactation, the

teats should be dipped with Chlordine dip for four

days after last milking. If the dip is visibly dirty or

contains sediment, use fresh solution.